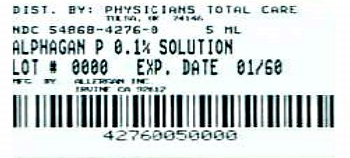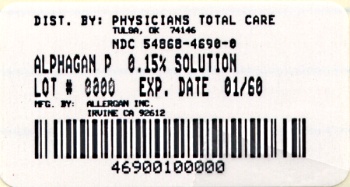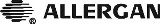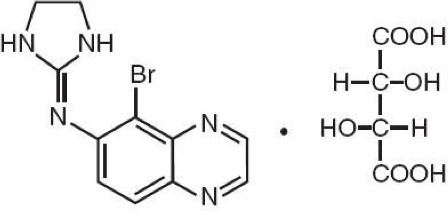 DRUG LABEL: ALPHAGAN P

NDC: 54868-4690 | Form: SOLUTION/ DROPS
Manufacturer: Physicians Total Care, Inc.
Category: prescription | Type: HUMAN PRESCRIPTION DRUG LABEL
Date: 20130315

ACTIVE INGREDIENTS: brimonidine tartrate
 1.5 mg/1 mL
INACTIVE INGREDIENTS: boric acid; calcium chloride; magnesium chloride; potassium chloride; water; sodium borate; carboxymethylcellulose sodium; sodium chloride; hydrochloric acid; sodium hydroxide

HIGHLIGHTS OF PRESCRIBING INFORMATION

These highlights do not include all the information needed to use ALPHAGAN® P safely and effectively. See full prescribing information for ALPHAGAN® P.
ALPHAGAN® P (brimonidine tartrate ophthalmic solution) 0.1% and 0.15%
Initial U.S. Approval: 1996

1 INDICATIONS AND USAGE

ALPHAGAN® P is an alpha adrenergic receptor agonist indicated for the reduction of elevated intraocular pressure (IOP) in patients with open-angle glaucoma or ocular hypertension. (1)

2 DOSAGE AND ADMINISTRATION

One drop in the affected eye(s), three times daily, approximately 8 hours apart. (2)

3 DOSAGE FORMS AND STRENGTHS

Solution containing 1 or 1.5 mg/mL brimonidine tartrate. (3)

4 CONTRAINDICATIONS

Neonates and infants (under the age of 2 years). (4.1)

5 WARNINGS AND PRECAUTIONS

Potentiation of vascular insufficiency. (5.1)

6 ADVERSE REACTIONS

Most common adverse reactions occurring in approximately 5% to 20% of patients receiving brimonidine ophthalmic solution (0.1%-0.2%) included allergic conjunctivitis, burning sensation, conjunctival folliculosis, conjunctival hyperemia, eye pruritus, hypertension, ocular allergic reaction, oral dryness, and visual disturbance. (6.1)

To report SUSPECTED ADVERSE REACTIONS, contact Allergan at 1-800-433-8871 or the FDA at 1-800-FDA-1088 or www.fda.gov/medwatch.

7 DRUG INTERACTIONS

- Antihypertensives/cardiac glycosides may lower blood pressure. (7.1)
- Use with CNS depressants may result in an additive or potentiating effect. (7.2)
- Tricyclic antidepressants may potentially blunt the hypotensive effect of systemic clonidine. (7.3)
- Monoamine oxidase inhibitors may result in increased hypotension. (7.4)

8 USE IN SPECIFIC POPULATIONS

Use with caution in children ≥ 2 years of age. (8.4)

FULL PRESCRIBING INFORMATION

1 INDICATIONS AND USAGE

ALPHAGAN® P (brimonidine tartrate ophthalmic solution) 0.1% or 0.15% is an alpha adrenergic receptor agonist indicated for the reduction of elevated intraocular pressure (IOP) in patients with open-angle glaucoma or ocular hypertension.

2 DOSAGE AND ADMINISTRATION

The recommended dose is one drop of ALPHAGAN® P in the affected eye(s) three times daily, approximately 8 hours apart. ALPHAGAN® P ophthalmic solution may be used concomitantly with other topical ophthalmic drug products to lower intraocular pressure. If more than one topical ophthalmic product is to be used, the different products should be instilled at least 5 minutes apart.

3 DOSAGE FORMS AND STRENGTHS

Solution containing 1 mg/mL or 1.5 mg/mL brimonidine tartrate.

4 CONTRAINDICATIONS

4.1 Neonates and Infants (under the age of 2 years)

ALPHAGAN® P is contraindicated in neonates and infants (under the age of 2 years).

4.2 Hypersensitivity Reactions

ALPHAGAN® P is contraindicated in patients who have exhibited a hypersensitivity reaction to any component of this medication in the past.

5 WARNINGS AND PRECAUTIONS

5.1 Potentiation of Vascular Insufficiency

ALPHAGAN® P may potentiate syndromes associated with vascular insufficiency. ALPHAGAN® P should be used with caution in patients with depression, cerebral or coronary insufficiency, Raynaud's phenomenon, orthostatic hypotension, or thromboangiitis obliterans.

5.2 Severe Cardiovascular Disease

Although brimonidine tartrate ophthalmic solution had minimal effect on the blood pressure of patients in clinical studies, caution should be exercised in treating patients with severe cardiovascular disease.

5.3 Contamination of Topical Ophthalmic Products After Use

There have been reports of bacterial keratitis associated with the use of multiple-dose containers of topical ophthalmic products. These containers had been inadvertently contaminated by patients who, in most cases, had a concurrent corneal disease or a disruption of the ocular epithelial surface (see PATIENT COUNSELING INFORMATION, 17).

6 ADVERSE REACTIONS

6.1 Clinical Studies Experience

Because clinical studies are conducted under widely varying conditions, adverse reaction rates observed in the clinical studies of a drug cannot be directly compared to rates in the clinical studies of another drug and may not reflect the rates observed in practice.

Adverse reactions occurring in approximately 10-20% of the subjects receiving brimonidine ophthalmic solution (0.1-0.2%) included: allergic conjunctivitis, conjunctival hyperemia, and eye pruritus. Adverse reactions occurring in approximately 5-9% included: burning sensation, conjunctival folliculosis, hypertension, ocular allergic reaction, oral dryness, and visual disturbance.

Adverse reactions occurring in approximately 1-4% of the subjects receiving brimonidine ophthalmic solution (0.1-0.2%) included: abnormal taste, allergic reaction, asthenia, blepharitis, blepharoconjunctivitis, blurred vision, bronchitis, cataract, conjunctival edema, conjunctival hemorrhage, conjunctivitis, cough, dizziness, dyspepsia, dyspnea, epiphora, eye discharge, eye dryness, eye irritation, eye pain, eyelid edema, eyelid erythema, fatigue, flu syndrome, follicular conjunctivitis, foreign body sensation, gastrointestinal disorder, headache, hypercholesterolemia, hypotension, infection (primarily colds and respiratory infections), insomnia, keratitis, lid disorder, pharyngitis, photophobia, rash, rhinitis, sinus infection, sinusitis, somnolence, stinging, superficial punctate keratopathy, tearing, visual field defect, vitreous detachment, vitreous disorder, vitreous floaters, and worsened visual acuity.

The following reactions were reported in less than 1% of subjects: corneal erosion, hordeolum, nasal dryness, and taste perversion.

6.2 Postmarketing Experience

The following reactions have been identified during postmarketing use of brimonidine tartrate ophthalmic solutions in clinical practice. Because they are reported voluntarily from a population of unknown size, estimates of frequency cannot be made. The reactions, which have been chosen for inclusion due to either their seriousness, frequency of reporting, possible causal connection to brimonidine tartrate ophthalmic solutions, or a combination of these factors, include: bradycardia, depression, hypersensitivity, iritis, keratoconjunctivitis sicca, miosis, nausea, skin reactions (including erythema, eyelid pruritus, rash, and vasodilation), syncope, and tachycardia. Apnea, bradycardia, coma, hypotension, hypothermia, hypotonia, lethargy, pallor, respiratory depression, and somnolence have been reported in infants receiving brimonidine tartrate ophthalmic solutions.

7 DRUG INTERACTIONS

7.1 Antihypertensives/Cardiac Glycosides

Because ALPHAGAN® P may reduce blood pressure, caution in using drugs such as antihypertensives and/or cardiac glycosides with ALPHAGAN® P is advised.

7.2 CNS Depressants

Although specific drug interaction studies have not been conducted with ALPHAGAN® P, the possibility of an additive or potentiating effect with CNS depressants (alcohol, barbiturates, opiates, sedatives, or anesthetics) should be considered.

7.3 Tricyclic Antidepressants

Tricyclic antidepressants have been reported to blunt the hypotensive effect of systemic clonidine. It is not known whether the concurrent use of these agents with ALPHAGAN® P in humans can lead to resulting interference with the IOP lowering effect. Caution is advised in patients taking tricyclic antidepressants which can affect the metabolism and uptake of circulating amines.

7.4 Monoamine Oxidase Inhibitors

Monoamine oxidase (MAO) inhibitors may theoretically interfere with the metabolism of brimonidine and potentially result in an increased systemic side-effect such as hypotension. Caution is advised in patients taking MAO inhibitors which can affect the metabolism and uptake of circulating amines.

8 USE IN SPECIFIC POPULATIONS

8.1 Pregnancy

Pregnancy Category B: Teratogenicity studies have been performed in animals.

Brimonidine tartrate was not teratogenic when given orally during gestation days 6 through 15 in rats and days 6 through 18 in rabbits. The highest doses of brimonidine tartrate in rats (2.5 mg/kg/day) and rabbits (5.0 mg/kg/day) achieved AUC exposure values 360- and 20-fold higher, or 260- and 15-fold higher, respectively, than similar values estimated in humans treated with ALPHAGAN® P 0.1% or 0.15%, 1 drop in both eyes three times daily.

There are no adequate and well-controlled studies in pregnant women; however, in animal studies, brimonidine crossed the placenta and entered into the fetal circulation to a limited extent. Because animal reproduction studies are not always predictive of human response, ALPHAGAN® P should be used during pregnancy only if the potential benefit to the mother justifies the potential risk to the fetus.

8.3 Nursing Mothers

It is not known whether brimonidine tartrate is excreted in human milk, although in animal studies, brimonidine tartrate has been shown to be excreted in breast milk. Because of the potential for serious adverse reactions from ALPHAGAN® P in nursing infants, a decision should be made whether to discontinue nursing or to discontinue the drug, taking into account the importance of the drug to the mother.

8.4 Pediatric Use

ALPHAGAN® P is contraindicated in children under the age of 2 years (see CONTRAINDICATIONS, 4.1). During postmarketing surveillance, apnea, bradycardia, coma, hypotension, hypothermia, hypotonia, lethargy, pallor, respiratory depression, and somnolence have been reported in infants receiving brimonidine. The safety and effectiveness of brimonidine tartrate have not been studied in children below the age of 2 years.

In a well-controlled clinical study conducted in pediatric glaucoma patients (ages 2 to 7 years) the most commonly observed adverse reactions with brimonidine tartrate ophthalmic solution 0.2% dosed three times daily were somnolence (50-83% in patients ages 2 to 6 years) and decreased alertness. In pediatric patients 7 years of age (>20 kg), somnolence appears to occur less frequently (25%). Approximately 16% of patients on brimonidine tartrate ophthalmic solution discontinued from the study due to somnolence.

8.5 Geriatric Use

No overall differences in safety or effectiveness have been observed between elderly and other adult patients.

8.6 Special Populations

ALPHAGAN® P has not been studied in patients with hepatic impairment.

ALPHAGAN® P has not been studied in patients with renal impairment. The effect of dialysis on brimonidine pharmacokinetics in patients with renal failure is not known.

10 OVERDOSAGE

Very limited information exists on accidental ingestion of brimonidine in adults; the only adverse reaction reported to date has been hypotension. Symptoms of brimonidine overdose have been reported in neonates, infants, and children receiving ALPHAGAN® P as part of medical treatment of congenital glaucoma or by accidental oral ingestion (see USE IN SPECIFIC POPULATIONS, 8.4). Treatment of an oral overdose includes supportive and symptomatic therapy; a patent airway should be maintained.

11 DESCRIPTION

ALPHAGAN® P (brimonidine tartrate ophthalmic solution) 0.1% or 0.15%, sterile, is a relatively selective alpha-2 adrenergic receptor agonist (topical intraocular pressure lowering agent).

The structural formula of brimonidine tartrate is:

5-Bromo-6-(2-imidazolidinylideneamino) quinoxaline L-tartrate; MW= 442.24

In solution, ALPHAGAN® P (brimonidine tartrate ophthalmic solution) has a clear, greenish-yellow color. It has an osmolality of 250-350 mOsmol/kg and a pH of 7.4-8.0 (0.1%) or 6.9-7.4 (0.15%).

Brimonidine tartrate appears as an off-white to pale-yellow powder and is soluble in both water (0.6 mg/mL) and in the product vehicle (1.4 mg/mL) at pH 7.7.

Each mL of ALPHAGAN® P contains the active ingredient brimonidine tartrate 0.1% (1 mg/mL) or 0.15% (1.5 mg/mL) with the inactive ingredients sodium carboxymethylcellulose; sodium borate; boric acid; sodium chloride; potassium chloride; calcium chloride; magnesium chloride; PURITE® 0.005% (0.05 mg/mL) as a preservative; purified water; and hydrochloric acid and/or sodium hydroxide to adjust pH.

12 CLINICAL PHARMACOLOGY

12.1 Mechanism of Action

ALPHAGAN® P is a relatively selective alpha-2 adrenergic receptor agonist with a peak ocular hypotensive effect occurring at two hours post-dosing.

Fluorophotometric studies in animals and humans suggest that brimonidine tartrate has a dual mechanism of action by reducing aqueous humor production and increasing uveoscleral outflow.

12.3 Pharmacokinetics

Absorption

After ocular administration of either a 0.1% or 0.2% solution, plasma concentrations peaked within 0.5 to 2.5 hours and declined with a systemic half-life of approximately 2 hours.

Distribution

The protein binding of brimonidine has not been studied.

Metabolism

In humans, brimonidine is extensively metabolized by the liver.

Excretion

Urinary excretion is the major route of elimination of brimonidine and its metabolites. Approximately 87% of an orally-administered radioactive dose of brimonidine was eliminated within 120 hours, with 74% found in the urine.

13 NONCLINICAL TOXICOLOGY

13.1 Carcinogenesis, Mutagenesis, Impairment of Fertility

No compound-related carcinogenic effects were observed in either mice or rats following a 21-month and 24-month study, respectively. In these studies, dietary administration of brimonidine tartrate at doses up to 2.5 mg/kg/day in mice and 1 mg/kg/day in rats achieved 150 and 120 times or 90 and 80 times, respectively, the plasma Cmax drug concentration in humans treated with one drop of ALPHAGAN® P 0.1% or 0.15% into both eyes 3 times per day, the recommended daily human dose.

Brimonidine tartrate was not mutagenic or clastogenic in a series of in vitro and in vivo studies including the Ames bacterial reversion test, chromosomal aberration assay in Chinese Hamster Ovary (CHO) cells, and three in vivo studies in CD-1 mice: a host-mediated assay, cytogenetic study, and dominant lethal assay.

Reproduction and fertility studies in rats with brimonidine tartrate demonstrated no adverse effect on male or female fertility at doses which achieve up to approximately 125 and 90 times the systemic exposure following the maximum recommended human ophthalmic dose of ALPHAGAN® P 0.1% or 0.15%, respectively.

14 CLINICAL STUDIES

Elevated IOP presents a major risk factor in glaucomatous field loss. The higher the level of IOP, the greater the likelihood of optic nerve damage and visual field loss. Brimonidine tartrate has the action of lowering intraocular pressure with minimal effect on cardiovascular and pulmonary parameters.

Clinical studies were conducted to evaluate the safety, efficacy, and acceptability of ALPHAGAN® P (brimonidine tartrate ophthalmic solution) 0.15% compared with ALPHAGAN® administered three-times-daily in patients with open-angle glaucoma or ocular hypertension. Those results indicated that ALPHAGAN® P (brimonidine tartrate ophthalmic solution) 0.15% is comparable in IOP lowering effect to ALPHAGAN® (brimonidine tartrate ophthalmic solution) 0.2%, and effectively lowers IOP in patients with open-angle glaucoma or ocular hypertension by approximately 2-6 mmHg.

A clinical study was conducted to evaluate the safety, efficacy, and acceptability of ALPHAGAN® P (brimonidine tartrate ophthalmic solution) 0.1% compared with ALPHAGAN® administered three-times-daily in patients with open-angle glaucoma or ocular hypertension. Those results indicated that ALPHAGAN® P (brimonidine tartrate ophthalmic solution) 0.1% is equivalent in IOP lowering effect to ALPHAGAN® (brimonidine tartrate ophthalmic solution) 0.2%, and effectively lowers IOP in patients with open-angle glaucoma or ocular hypertension by approximately 2-6 mmHg.

16 HOW SUPPLIED/STORAGE AND HANDLING

ALPHAGAN® P is supplied sterile, in teal opaque plastic LDPE bottles and tips, with purple high impact polystyrene (HIPS) caps as follows:

0.1%
5 mL in 10 mL bottle NDC 54868-4276-0
0.15%

5 mL in 10 mL bottle NDC 54868-4690-2
10 mL in 10 mL bottle NDC 54868-4690-0

STORAGE AND HANDLING

Storage: Store at 15°-25°C (59°-77°F).

17 PATIENT COUNSELING INFORMATION

Patients should be instructed that ocular solutions, if handled improperly or if the tip of the dispensing container contacts the eye or surrounding structures, can become contaminated by common bacteria known to cause ocular infections. Serious damage to the eye and subsequent loss of vision may result from using contaminated solutions (see WARNINGS AND PRECAUTIONS, 5.3). Always replace the cap after using. If solution changes color or becomes cloudy, do not use. Do not use the product after the expiration date marked on the bottle.

Patients also should be advised that if they have ocular surgery or develop an intercurrent ocular condition (e.g., trauma or infection), they should immediately seek their physician's advice concerning the continued use of the present multidose container.

If more than one topical ophthalmic drug is being used, the drugs should be administered at least five minutes apart.

As with other similar medications, ALPHAGAN® P may cause fatigue and/or drowsiness in some patients. Patients who engage in hazardous activities should be cautioned of the potential for a decrease in mental alertness.

© 2011 Allergan, Inc.
Irvine, CA 92612, U.S.A.
® marks owned by Allergan, Inc.
U.S. Patents 6,562,873; 6,627,210; 6,641,834; and 6,673,337

71816US15C

Additional bar code label applied by:
Physicians Total Care, Inc.
Tulsa, Oklahoma 74146

PACKAGE LABEL

Alphagan ® P

(brimonidine tartrate ophthalmic solution) 0.15%

10 mL sterile

NDC 54868-4690-0

Rx Only

Alphagan ® P

(brimonidine tartrate ophthalmic solution) 0.1%

5 mL sterile

NDC 54868-4276-0
Rx Only